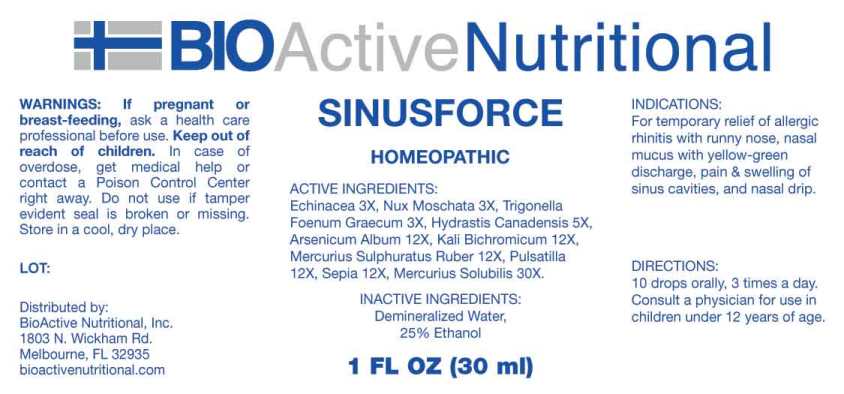 DRUG LABEL: Sinusforce
NDC: 43857-0616 | Form: LIQUID
Manufacturer: BioActive Nutritional, Inc.
Category: homeopathic | Type: HUMAN OTC DRUG LABEL
Date: 20240912

ACTIVE INGREDIENTS: ECHINACEA ANGUSTIFOLIA WHOLE 3 [hp_X]/1 mL; NUTMEG 3 [hp_X]/1 mL; FENUGREEK SEED 3 [hp_X]/1 mL; GOLDENSEAL 5 [hp_X]/1 mL; ARSENIC TRIOXIDE 12 [hp_X]/1 mL; POTASSIUM DICHROMATE 12 [hp_X]/1 mL; MERCURIC SULFIDE 12 [hp_X]/1 mL; PULSATILLA VULGARIS WHOLE 12 [hp_X]/1 mL; SEPIA OFFICINALIS JUICE 12 [hp_X]/1 mL; MERCURIUS SOLUBILIS 30 [hp_X]/1 mL
INACTIVE INGREDIENTS: WATER; ALCOHOL

DRUG FACTS:

ACTIVE INGREDIENTS:

Echinacea (Angustifolia) 3X, Nux Moschata 3X, Trigonella Foenum-Graecum 3X, Hydrastis Canadensis 5X, Arsenicum Album 12X, Kali Bichromicum 12X, Mercurius Sulphuratus Ruber 12X, Pulsatilla (Vulgaris) 12X, Sepia 12X, Mercurius Solubilis 30X.

INDICATIONS:

For temporary relief of allergic rhinitis with runny nose, nasal mucus with yellow-green discharge, pain & swelling of sinus cavities, and nasal drip.

WARNINGS:

If pregnant or breast-feeding, ask a health care professional before use.

Keep out of reach of children. In case of overdose, get medical help or contact a Poison Control Center right away.

Do not use if tamper evident seal is broken or missing.

Store in cool, dry place.

KEEP OUT OF REACH OF CHILDREN:

In case of overdose, get medical help or contact a Poison Control Center right away.

DIRECTIONS:

10 drops orally, 3 times a day. Consult a physician for use in children under 12 years of age.

INDICATIONS:

For temporary relief of allergic rhinitis with runny nose, nasal mucus with yellow-green discharge, pain & swelling of sinus cavities, and nasal drip.

INACTIVE INGREDIENTS:

Demineralized Water, 25% Ethanol

QUESTIONS:

Distributed by:
BioActive Nutritional, Inc.
1803 N. Wickham Rd.
Melbourne, FL 32935
bioactivenutritional.com

PACKAGE LABEL DISPLAY:

BIOActive Nutritional

SINUSFORCE

HOMEOPATHIC

1 FL OZ (30ml)